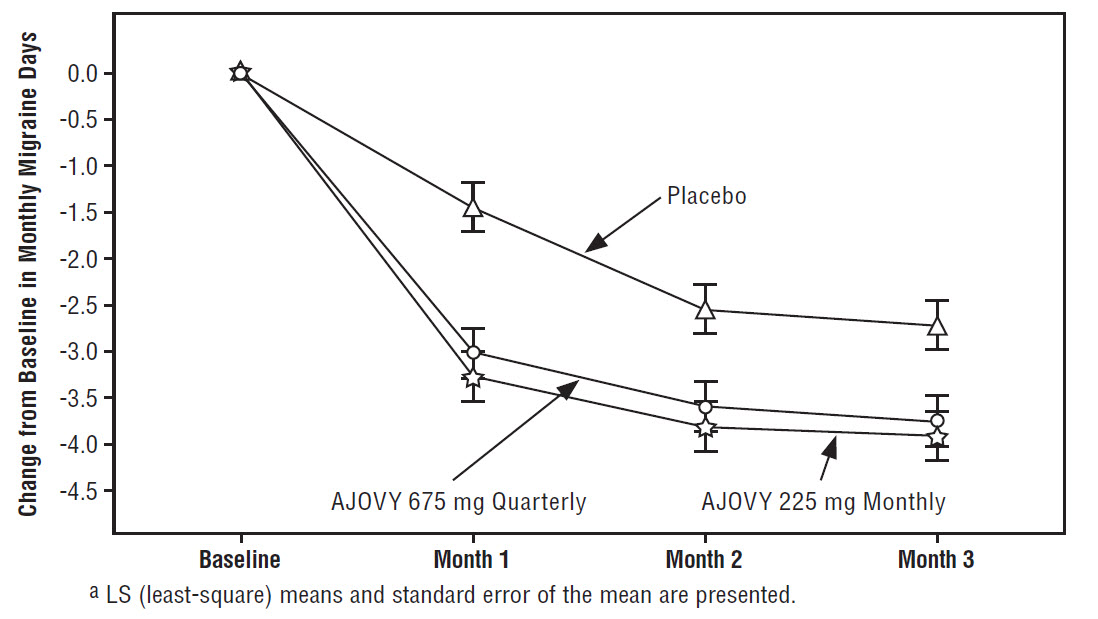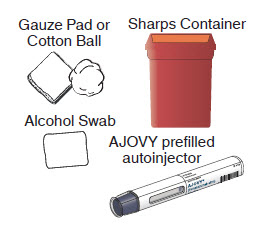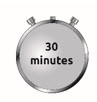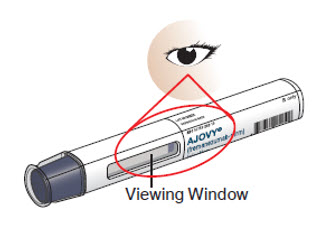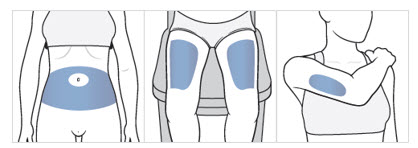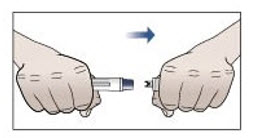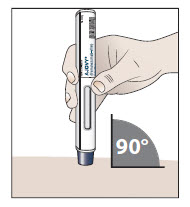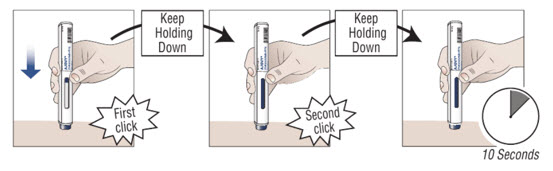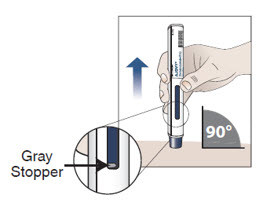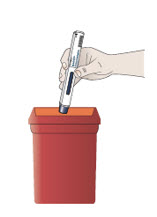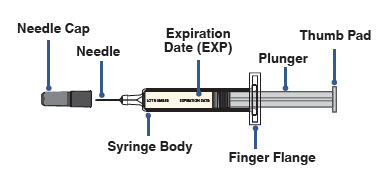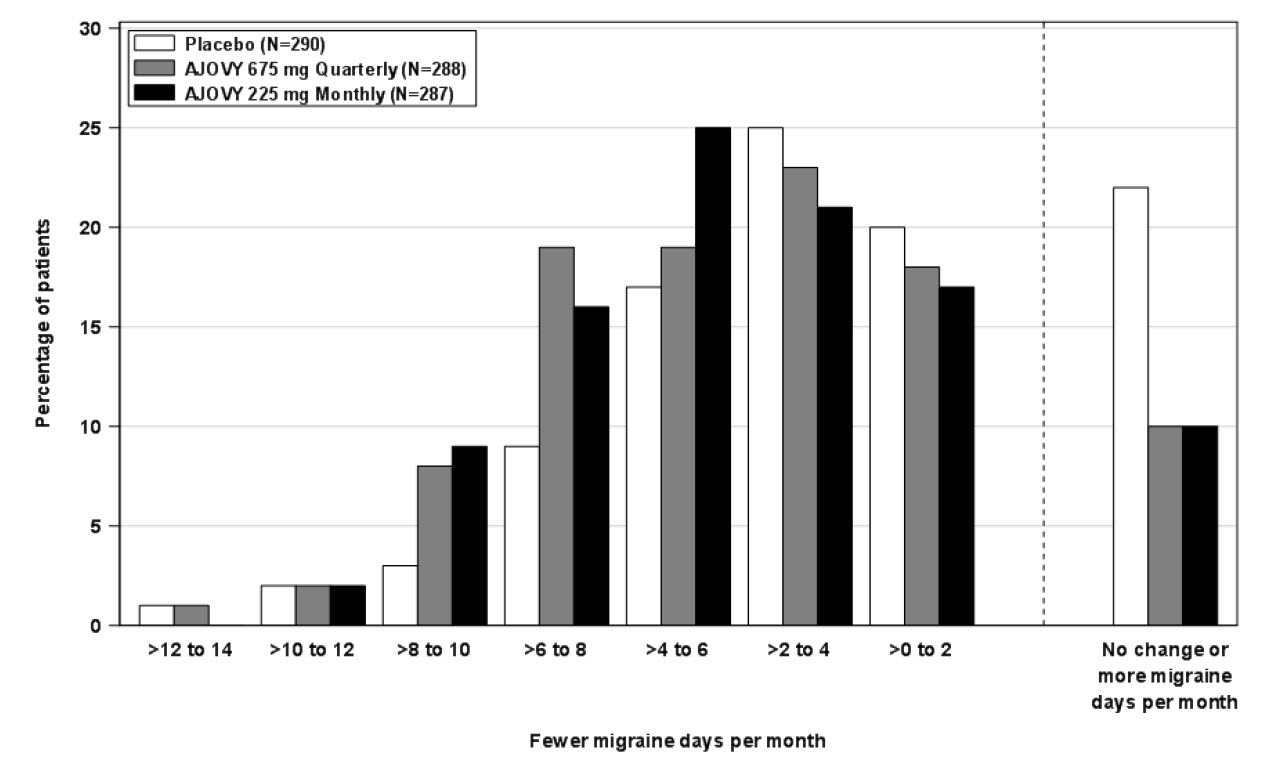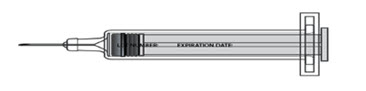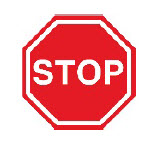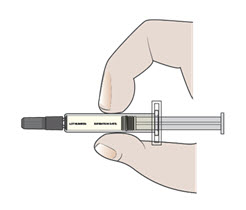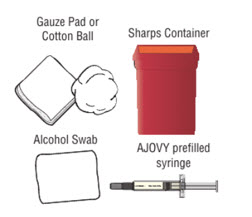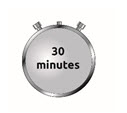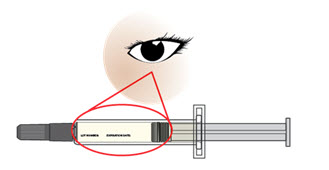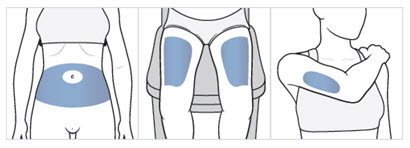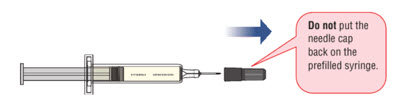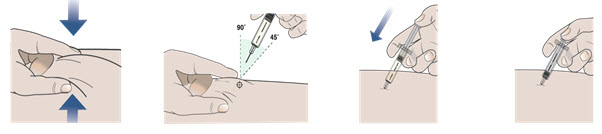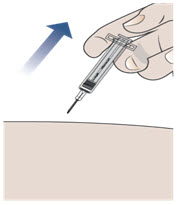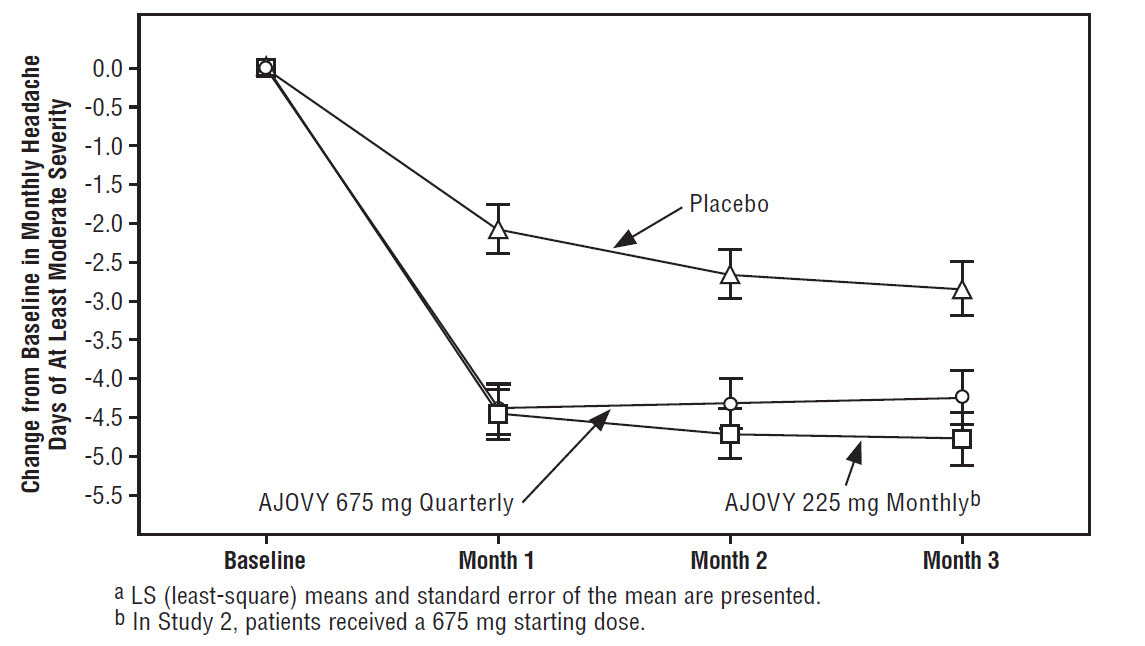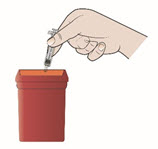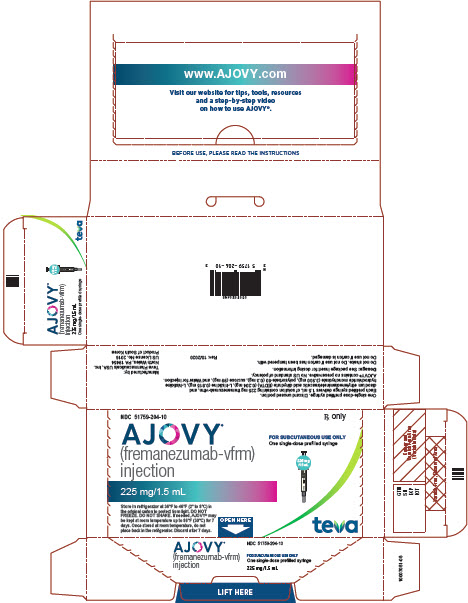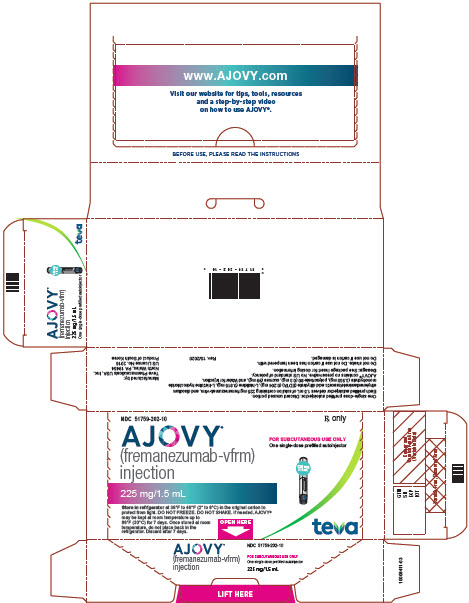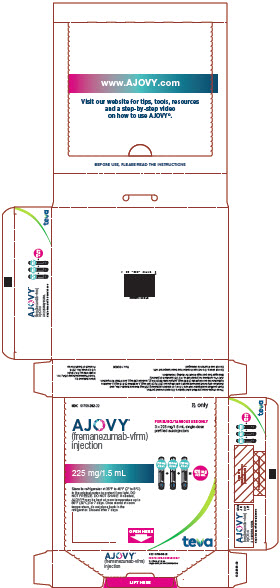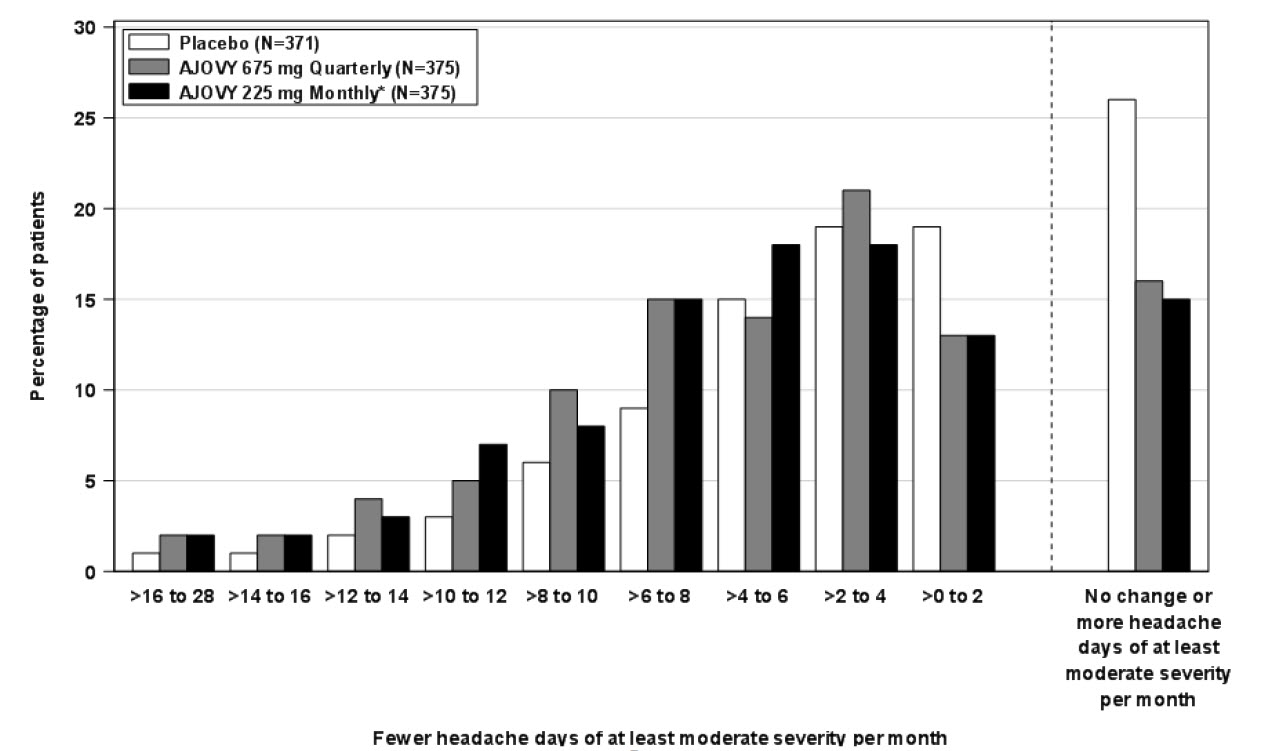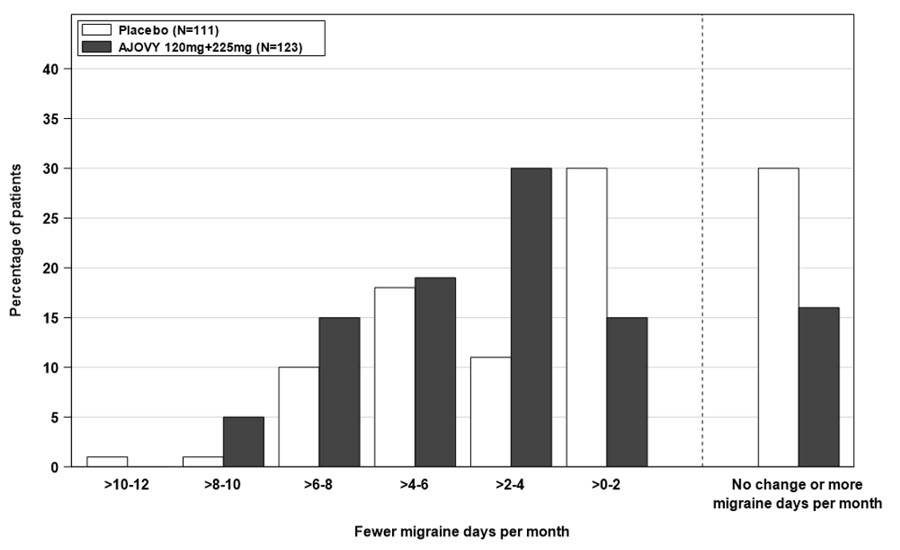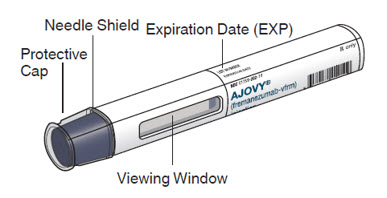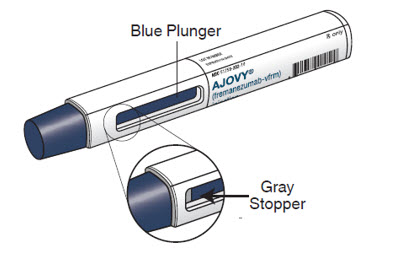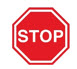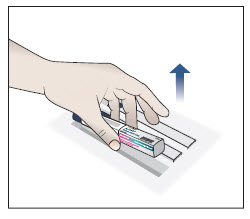 DRUG LABEL: AJOVY
NDC: 51759-204 | Form: INJECTION
Manufacturer: Teva Pharmaceuticals USA, Inc.
Category: prescription | Type: HUMAN PRESCRIPTION DRUG LABEL
Date: 20250805

ACTIVE INGREDIENTS: FREMANEZUMAB 225 mg/1.5 mL
INACTIVE INGREDIENTS: SUCROSE; HISTIDINE; POLYSORBATE 80; DISODIUM ETHYLENEDIAMINEDIACETATE; WATER

HIGHLIGHTS OF PRESCRIBING INFORMATION

These highlights do not include all the information needed to use AJOVY safely and effectively. See full prescribing information for AJOVY.
AJOVY® (fremanezumab-vfrm) injection, for subcutaneous use
Initial U.S. Approval: 2018

RECENT MAJOR CHANGES

Indications and Usage (1) 8/2025

Dosage and Administration (2.1, 2.2) 8/2025

Warnings and Precautions (5.2, 5.3) 3/2025

1 INDICATIONS AND USAGE

AJOVY is a calcitonin gene-related peptide antagonist indicated for:

- the preventive treatment of migraine in adults, and
- the preventive treatment of episodic migraine in pediatric patients who are 6 to 17 years of age and who weigh 45 kg or more. (1)

2 DOSAGE AND ADMINISTRATION

For subcutaneous use only. Recommended dosage:

- Adults: Two subcutaneous dosing options of AJOVY are available to administer the recommended dosage; 225 mg monthly or 675 mg every 3 months (quarterly). The 675 mg quarterly dosage is administered as three consecutive injections of 225 mg each. (2.1)
- Pediatric patients 6 to 17 years of age and who weigh 45 kg or more: 225 mg monthly (2.1)

Administer in the abdomen, thigh, or upper arm subcutaneously. (2.2)

See Dosage and Administration for important administration instructions. (2.2)

3 DOSAGE FORMS AND STRENGTHS

Injection: 225 mg/1.5 mL solution in a single-dose prefilled autoinjector. (3)

Injection: 225 mg/1.5 mL solution in a single-dose prefilled syringe. (3)

4 CONTRAINDICATIONS

AJOVY is contraindicated in patients with serious hypersensitivity to fremanezumab-vfrm or to any of the excipients. (4)

5 WARNINGS AND PRECAUTIONS

- Hypersensitivity Reactions: Most reactions were reported from within hours to one month after administration. If hypersensitivity occurs, consider discontinuing AJOVY and institute appropriate therapy. (5.1)
- Hypertension: New-onset or worsening of pre-existing hypertension may occur. (5.2)
- Raynaud's Phenomenon: New-onset or worsening of pre-existing Raynaud’s phenomenon may occur. (5.3)

6 ADVERSE REACTIONS

The most common adverse reactions (≥5% and greater than placebo) were injection site reactions. (6.1)

To report SUSPECTED ADVERSE REACTIONS, contact Teva Pharmaceuticals at 1-888-483-8279 or FDA at 1-800-FDA-1088 or www.fda.gov/medwatch.

FULL PRESCRIBING INFORMATION

1 INDICATIONS AND USAGE

AJOVY is indicated for:

- the preventive treatment of migraine in adults, and
- the preventive treatment of episodic migraine in pediatric patients who are 6 to 17 years of age and who weigh 45 kg or more.

2 DOSAGE AND ADMINISTRATION

2.1 Recommended Dosage

Adults

The recommended dosage in adults for the preventive treatment of migraine is administered by subcutaneous injection as one of the following options:

- 225 mg monthly, or
- 675 mg every 3 months (quarterly), which is administered as three consecutive subcutaneous injections of 225 mg each.

When switching dosage options, administer the first dose of the new regimen on the next scheduled date of administration.

Pediatric Patients who are 6 to 17 Years of Age and who Weigh 45 kg or More:

The recommended dosage for the preventive treatment of episodic migraine in pediatric patients who are 6 to 17 years of age and who weigh 45 kg or more is administered by subcutaneous injection as follows:

- 225 mg monthly.

AJOVY is not approved in pediatric patients weighing less than 45 kg because of the lack of an appropriate strength presentation [see Clinical Studies (14) and How Supplied/Storage and Handling (16.1)].

Missed Dose

If a dose of AJOVY is missed, administer as soon as possible. Thereafter, AJOVY can be scheduled from the date of the last dose.

2.2 Important Administration Instructions

AJOVY is for subcutaneous use only.

AJOVY may be administered by healthcare providers, patients 13 years of age and older, and/or caregivers. In pediatric patients 6 to 12 years of age, AJOVY must be administered by a healthcare provider or adult caregiver. Prior to use, provide proper training to patients and/or caregivers on the preparation and administration of AJOVY prefilled syringe, including aseptic technique [see Instructions for Use]:

- Remove AJOVY from the refrigerator. Prior to use, allow AJOVY to sit at room temperature for 30 minutes protected from direct sunlight. Do not warm by using a heat source such as hot water or a microwave. Do not use AJOVY if it has been at room temperature for 7 days or longer [see How Supplied/Storage and Handling (16.2)].
- Follow aseptic injection technique every time AJOVY is administered.
- Inspect AJOVY for particles or discoloration prior to administration [see Dosage Forms and Strengths (3)]. Do not use if the solution is cloudy, discolored, or contains particles.
- Administer AJOVY by subcutaneous injection into areas of the abdomen, thigh, or upper arm that are not tender, bruised, red, or indurated. For multiple injections, you may use the same body site, but not the exact location of the previous injection.
- Do not co-administer AJOVY with other injectable drugs at the same injection site.

3 DOSAGE FORMS AND STRENGTHS

AJOVY is a sterile, clear to opalescent, colorless to slightly yellow solution, available as follows:

- Injection: 225 mg/1.5 mL single-dose prefilled autoinjector
- Injection: 225 mg/1.5 mL single-dose prefilled syringe

4 CONTRAINDICATIONS

AJOVY is contraindicated in patients with serious hypersensitivity to fremanezumab-vfrm or to any of the excipients. Reactions have included anaphylaxis and angioedema [see Warnings and Precautions (5.1)].

5 WARNINGS AND PRECAUTIONS

5.1 Hypersensitivity Reactions

Hypersensitivity reactions, including rash, pruritus, drug hypersensitivity, and urticaria, were reported with AJOVY in clinical trials. Most reactions were mild to moderate, but some led to discontinuation or required corticosteroid treatment. Most reactions were reported from within hours to one month after administration. Cases of anaphylaxis and angioedema have been reported in the postmarketing setting.

If a hypersensitivity reaction occurs, consider discontinuing AJOVY, and institute appropriate therapy [see Contraindications (4)].

5.2 Hypertension

Development of hypertension and worsening of pre-existing hypertension have been reported following the use of CGRP antagonists, including AJOVY, in the postmarketing setting. Some of the patients who developed new-onset hypertension had risk factors for hypertension. There were cases requiring initiation of pharmacological treatment for hypertension and, in some cases, hospitalization. Hypertension may occur at any time during treatment, but was most frequently reported within 7 days of therapy initiation. AJOVY was discontinued in many of the reported cases.

Monitor patients treated with AJOVY for new-onset hypertension or worsening of pre-existing hypertension, and consider whether discontinuation of AJOVY is warranted if evaluation fails to establish an alternative etiology or blood pressure is inadequately controlled.

5.3 Raynaud's Phenomenon

Development of Raynaud’s phenomenon and recurrence or worsening of pre-existing Raynaud’s phenomenon have been reported in the postmarketing setting following the use of CGRP antagonists, including AJOVY. In reported cases with monoclonal antibody CGRP antagonists, symptom onset occurred a median of 71 days following dosing. Many of the cases reported serious outcomes, including hospitalizations and disability, generally related to debilitating pain.

In most reported cases, discontinuation of the CGRP antagonist resulted in resolution of symptoms.

AJOVY should be discontinued if signs or symptoms of Raynaud’s phenomenon develop and patients should be evaluated by a healthcare provider if symptoms do not resolve. Patients with a history of Raynaud’s phenomenon should be monitored for, and informed about the possibility of, worsening or recurrence of signs and symptoms.

6 ADVERSE REACTIONS

The following clinically significant adverse reactions are discussed in greater detail in other sections of the labeling:

- Hypersensitivity Reactions [see Warnings and Precautions (5.1)]
- Hypertension [see Warnings and Precautions (5.2)]
- Raynaud’s Phenomenon [see Warnings and Precautions (5.3)]

6.1 Clinical Trials Experience

Because clinical trials are conducted under widely varying conditions, adverse reaction rates observed in the clinical trials of a drug cannot be directly compared to rates in the clinical trials of another drug, and may not reflect the rates observed in clinical practice.

Adults

The safety of AJOVY was evaluated in 2512 patients with migraine who received at least 1 dose of AJOVY, representing 1279 patient-years of exposure. Of these, 1730 patients were exposed to AJOVY 225 mg monthly or AJOVY 675 mg quarterly for at least 6 months, 775 patients for at least 12 months, and 138 patients for at least 15 months. In placebo-controlled clinical trials (Studies 1 and 2), 662 patients received AJOVY 225 mg monthly for 12 weeks (with or without a loading dose of 675 mg), and 663 patients received AJOVY 675 mg quarterly for 12 weeks [see Clinical Studies (14)]. In the controlled trials, 87% of patients were female, 80% were White, and the mean age was 41 years.

The most common adverse reactions in the clinical trials for the preventive treatment of migraine (incidence at least 5% and greater than placebo) were injection site reactions. The adverse reactions that most commonly led to discontinuations were injection site reactions (1%). Table 1 summarizes adverse reactions reported in the 3-month placebo-controlled studies (Study 1 and Study 2), and the 1-month follow-up period after those studies.

Table 1: Adverse Reactions Occurring with an Incidence of At Least 2% for Either Dosing Regimen of AJOVY and At Least 2% Greater Than Placebo in Studies 1 and 2
Adverse Reaction | AJOVY 225 mg Monthly (n=290) % | AJOVY 675 mg Quarterly (n=667) % | Placebo Monthly (n=668) %
Injection site reactionsa | 43 | 45 | 38

a Injection site reactions include multiple related adverse event terms, such as injection site pain, induration, and erythema.

Pediatric Patients 6 to 17 Years of Age

The safety of AJOVY was evaluated in 225 pediatric patients 6 to 17 years of age with episodic migraine who received at least one dose of AJOVY. Of these patients, 209 received AJOVY monthly for at least 6 months and 100 received AJOVY for at least 12 months. In the placebo-controlled trial (Study 3), 123 pediatric patients with episodic migraine were treated with AJOVY [see Clinical Studies (14)]. The most common adverse reactions of AJOVY observed in Study 3 were injection site reactions. Hypersensitivity reactions were also observed. Overall, the safety profile in pediatric patients is similar to the known safety profile in adults.

6.2 Postmarketing Experience

The following adverse reactions have been identified during postapproval use of AJOVY. Because these reactions are reported voluntarily from a population of uncertain size, it is not always possible to reliably estimate their frequency or establish a causal relationship to drug exposure.

Immune System Disorders: Anaphylactic reactions and angioedema [see Contraindications (4) and Warnings and Precautions (5.1)]

Vascular Disorders: Hypertension [see Warnings and Precautions (5.2)], Raynaud’s phenomenon [see Warnings and Precautions (5.3)]

8 USE IN SPECIFIC POPULATIONS

8.1 Pregnancy

Pregnancy Exposure Registry

There is a pregnancy exposure registry that monitors pregnancy outcomes in women exposed to AJOVY during pregnancy. Healthcare providers are encouraged to register pregnant patients, or pregnant women may enroll themselves in the registry by calling 1-833-927-2605 or visiting www.tevamigrainepregnancyregistry.com.

Risk Summary

There are no adequate data on the developmental risk associated with the use of AJOVY in pregnant women. AJOVY has a long half-life [see Clinical Pharmacology (12.3)]. This should be taken into consideration for women who are pregnant or plan to become pregnant while using AJOVY. Administration of fremanezumab-vfrm to rats and rabbits during the period of organogenesis or to rats throughout pregnancy and lactation at doses resulting in plasma levels greater than those expected clinically did not result in adverse effects on development [see Animal Data]. In the U.S. general population, the estimated background risk of major birth defects and miscarriage in clinically recognized pregnancies is 2-4% and 15-20%, respectively. The estimated rate of major birth defects (2.2-2.9%) and miscarriage (17%) among deliveries to women with migraine are similar to rates reported in women without migraine.

Clinical Considerations

Disease-Associated Maternal and/or Embryo/Fetal Risk

Published data have suggested that women with migraine may be at increased risk of preeclampsia and gestational hypertension during pregnancy.

Data

Animal Data

When fremanezumab-vfrm (0, 50, 100, or 200 mg/kg) was administered to male and female rats by weekly subcutaneous injection prior to and during mating and continuing in females throughout organogenesis, no adverse embryofetal effects were observed. The highest dose tested was associated with plasma exposures (AUC) approximately 2 times that in humans at a dose of 675 mg.

Administration of fremanezumab-vfrm (0, 10, 50, or 100 mg/kg) weekly by subcutaneous injection to pregnant rabbits throughout the period of organogenesis produced no adverse effects on embryofetal development. The highest dose tested was associated with plasma AUC approximately 3 times that in humans (675 mg).

Administration of fremanezumab-vfrm (0, 50, 100, or 200 mg/kg) weekly by subcutaneous injection to female rats throughout pregnancy and lactation resulted in no adverse effects on pre- and postnatal development. The highest dose tested was associated with plasma AUC approximately 2 times that in humans (675 mg).

8.2 Lactation

Risk Summary

There are no data on the presence of fremanezumab-vfrm in human milk, the effects on the breastfed infant, or the effects on milk production. The developmental and health benefits of breastfeeding should be considered along with the mother’s clinical need for AJOVY and any potential adverse effects on the breastfed infant from AJOVY or from the underlying maternal condition.

8.4 Pediatric Use

Episodic Migraine

The safety and effectiveness of AJOVY have been established in an adequate and well-controlled study for the preventive treatment of episodic migraine in pediatric patients who are 6 to 17 years of age and who weigh 45 kg or more (Study 3). The safety and efficacy profile of AJOVY in these patients was similar to the safety and efficacy profile seen in clinical trials in adults with migraine [see Adverse Reactions (6.1), Clinical Pharmacology (12.3), and Clinical Studies (14)].

AJOVY is not approved in pediatric patients weighing less than 45 kg because of the lack of an appropriate strength presentation.

The safety and effectiveness of AJOVY for the preventive treatment of episodic migraine in pediatric patients younger than 6 years of age have not been established.

Chronic Migraine

The safety and effectiveness of AJOVY for the preventive treatment of chronic migraine in pediatric patients have not been established.

Juvenile Animal Toxicity Data

Subcutaneous administration of fremanezumab-vfrm (0, 50, 150, or 450 mg/kg) to juvenile rats once weekly from postnatal day (PND) 28 to PND 63 resulted in no adverse effects on growth, sexual maturation, or neurobehavioral or reproductive function. The highest dose tested was associated with plasma drug exposures (AUC) approximately 58 times that in pediatric patients at the recommended human dose (225 mg), when calculated on a monthly basis.

8.5 Geriatric Use

Clinical studies of AJOVY did not include sufficient numbers of subjects aged 65 and over to determine whether they respond differently from younger subjects.

11 DESCRIPTION

Fremanezumab-vfrm is a humanized IgG2Δa/kappa monoclonal antibody specific for calcitonin gene-related peptide (CGRP) ligand. Fremanezumab-vfrm is produced by recombinant DNA technology in Chinese hamster ovary (CHO) cells. The antibody consists of 1324 amino acids and has a molecular weight of approximately 148 kDa.

AJOVY (fremanezumab-vfrm) injection is a sterile, preservative-free, clear to opalescent, colorless to slightly yellow solution for subcutaneous injection, supplied in a single-dose 225 mg/1.5 mL prefilled autoinjector and a single-dose 225 mg/1.5 mL prefilled syringe.

Each prefilled autoinjector or prefilled syringe delivers 1.5 mL of solution containing 225 mg fremanezumab-vfrm, disodium ethylenediaminetetraacetic acid dihydrate (EDTA) (0.204 mg), L-histidine (0.815 mg), L-histidine hydrochloride monohydrate (3.93 mg), polysorbate-80 (0.3 mg), sucrose (99 mg), and Water for Injection, and has a pH of 5.5.

12 CLINICAL PHARMACOLOGY

12.1 Mechanism of Action

Fremanezumab-vfrm is a humanized monoclonal antibody that binds to calcitonin gene-related peptide (CGRP) ligand and blocks its binding to the receptor.

12.2 Pharmacodynamics

The relationship between the pharmacodynamic activity and the mechanism(s) by which fremanezumab-vfrm exerts its clinical effects is unknown.

12.3 Pharmacokinetics

Absorption

After single subcutaneous (SC) administrations of 225 mg, 675 mg, and 900 mg fremanezumab-vfrm, median time to maximum concentrations (tmax) was 5 to 7 days. Dose-proportionality, based on population PK, was observed between 225 mg to 900 mg. The geometric mean (%CV) for fremanezumab-vfrm maximum concentration (Cmax) was 29.7 (13.7%) µg/mL and total systemic exposure (AUC0-inf) was 42.5 (17.5%) h*mg/mL following administration of 225 mg fremanezumab-vfrm. The geometric mean (%CV) for fremanezumab-vfrm maximum concentration (Cmax) was 104.8 (28.8%) µg/mL and total systemic exposure (AUC0-inf) was 132.8 (31.7%) h*mg/mL following administration of 675 mg fremanezumab-vfrm. Steady state was achieved by approximately 168 days (approximately 6 months) following 225 mg SC monthly and 675 mg SC quarterly dosing regimens. Median accumulation ratio, based on once-monthly and once-quarterly dosing regimens, is approximately 2.3 and 1.2, respectively.

Distribution

Fremanezumab-vfrm has an apparent volume of distribution of approximately 6 liters, suggesting minimal distribution to the extravascular tissues.

Metabolism

Similar to other monoclonal antibodies, fremanezumab-vfrm is degraded by enzymatic proteolysis into small peptides and amino acids.

Elimination

Fremanezumab-vfrm apparent clearance was approximately 0.141 L/day. Fremanezumab-vfrm was estimated to have a half-life of approximately 31 days.

Specific Populations

No clinically significant differences in fremanezumab-vfrm pharmacokinetics were predicted based on race (White, Black, Asian, and other races), sex, mild hepatic impairment (Child-Pugh Class A), and moderate hepatic impairment (Child-Pugh Class B). The effect of severe hepatic impairment (Child-Pugh Class C) on fremanezumab-vfrm pharmacokinetics is unknown.

Pediatric Patients

Following subcutaneous administration of 225 mg AJOVY monthly in the pediatric population weighing 45 kg or more, the predicted steady state fremanezumab-vfrm exposures (maximum plasma concentration [Cmax], area under the plasma concentration-time curve [AUC]) are similar to those of adults.

Drug Interactions

Fremanezumab is not metabolized by cytochrome P450 enzymes; therefore, interactions with concomitant medications that are substrates, inducers, or inhibitors of cytochrome P450 enzymes are unlikely. Additionally, the effects of medications for the acute treatment (specifically analgesics, ergots, and triptans) and preventive treatment of migraine were evaluated in a population PK model, and found not to influence fremanezumab exposure.

12.6 Immunogenicity

The observed incidence of anti-drug antibodies is highly dependent on the sensitivity and specificity of the assay. Differences in assay methods preclude meaningful comparisons of the incidence of anti-drug antibodies in the studies described below with the incidence of anti-drug antibodies in other studies, including those of fremanezumab-vfrm or of other fremanezumab products.

In 3-month, placebo-controlled studies in adult patients, treatment-emergent anti-drug antibodies were observed in 0.4% (6 out of 1701) AJOVY-treated patients. One of the 6 patients developed anti-AJOVY neutralizing antibodies at Day 84. In the long-term, open-label study, anti-drug antibodies were detected in 1.6% of patients (30 out of 1888). Out of 30 anti-drug antibody-positive patients, 17 had a neutralizing activity in their post-dose samples. Although these data do not demonstrate an impact of anti-fremanezumab-vfrm antibody development on efficacy or safety of AJOVY in these patients, available data are too limited to make definitive conclusions.

In the 3-month, placebo-controlled study in pediatric patients with episodic migraine, treatment-emergent anti-drug antibody responses were observed in 2 out of 123 (1.6%) AJOVY-treated patients. One of the 2 patients developed anti-fremanezumab-vfrm neutralizing antibodies at Day 84. The available data are too limited to make definitive conclusions about the impact of the development of anti-fremanezumab-vfrm antibodies on the pharmacokinetics, efficacy, or safety of AJOVY in pediatric patients.

13 NONCLINICAL TOXICOLOGY

13.1 Carcinogenesis, Mutagenesis, Impairment of Fertility

Carcinogenesis

Carcinogenicity studies of fremanezumab-vfrm were not conducted.

Mutagenesis

Genetic toxicology studies of fremanezumab-vfrm were not conducted.

Impairment of Fertility

When fremanezumab-vfrm (0, 50, 100, or 200 mg/kg) was administered to male and female rats by weekly subcutaneous injection prior to and during mating and continuing in females throughout organogenesis, no adverse effects on male or female fertility were observed. The highest dose tested was associated with plasma exposures (AUC) approximately 2 times that in humans at a dose of 675 mg.

14 CLINICAL STUDIES

Adults

The efficacy of AJOVY was evaluated as a preventive treatment of episodic or chronic migraine in adult patients in two multicenter, randomized, 3-month, double-blind, placebo-controlled studies (Study 1 and Study 2, respectively).

Episodic Migraine

Study 1 (NCT 02629861) included adults with a history of episodic migraine (patients with <15 headache days per month). All patients were randomized (1:1:1) to receive subcutaneous injections of either AJOVY 675 mg every three months (quarterly), AJOVY 225 mg monthly, or placebo monthly, over a 3-month treatment period. Patients were allowed to use acute headache treatments during the study. A subset of patients (21%) was allowed to use one additional concomitant preventive medication.

The study excluded patients with a history of significant cardiovascular disease, vascular ischemia, or thrombotic events, such as cerebrovascular accident, transient ischemic attacks, deep vein thrombosis, or pulmonary embolism.

The primary efficacy endpoint was the mean change from baseline in the monthly average number of migraine days during the 3-month treatment period. Secondary endpoints included the proportion of patients reaching at least a 50% reduction in monthly average number of migraine days during the 3-month treatment period, the mean change from baseline in the monthly average number of days of use of any acute headache medication during the 3-month treatment period, and the mean change from baseline in the number of migraine days during the first month of the treatment period.

In Study 1, a total of 875 patients (742 females, 133 males), ranging in age from 18 to 70 years, were randomized. A total of 791 patients completed the 3-month double-blind phase. The mean migraine frequency at baseline was approximately 9 migraine days per month, and was similar across treatment groups.

Both monthly and quarterly dosing regimens of AJOVY demonstrated statistically significant improvements for efficacy endpoints compared to placebo over the 3-month period, as summarized in Table 3.

Table 3: Efficacy Endpoints in Study 1
Study 1 Efficacy Endpoint | AJOVY 225 mg Monthly (N=287) | AJOVY 675 mg Quarterly (N=288) | Placebo (N=290)
Monthly migraine days (MMD)
Baseline migraine days | 8.9 | 9.2 | 9.1
Change from baseline | -3.7 | -3.4 | -2.2
Difference from placebo | -1.5 | -1.2
p-value | <0.001 | <0.001
≥50% MMD responders
% responders | 47.7% | 44.4% | 27.9%
Difference from placebo | 19.8% | 16.5%
p-value | <0.001 | <0.001
Monthly acute headache medication days
Change from baseline | -3.0 | -2.9 | -1.6
Difference from placebo | -1.4 | -1.3
p-value | <0.001 | <0.001

Figure 1 displays the mean change from baseline in the average monthly number of migraine days in Study 1.

Figure 1: Change from Baseline in Monthly Migraine Days in Study 1a

Figure 2 shows the distribution of change from baseline in mean monthly migraine days in bins of 2 days by treatment group in Study 1. A treatment benefit over placebo for both doses of AJOVY is seen across a range of changes from baseline in monthly migraine days.

Figure 2: Distribution of Change from Baseline in Mean Monthly Migraine Days by Treatment Group in Study 1

Chronic Migraine

Study 2 (NCT 02621931) included adults with a history of chronic migraine (patients with ≥15 headache days per month). All patients were randomized (1:1:1) to receive subcutaneous injections of either AJOVY 675 mg starting dose followed by 225 mg monthly, 675 mg every 3 months (quarterly), or placebo monthly, over a 3-month treatment period. Patients were allowed to use acute headache treatments during the study. A subset of patients (21%) was allowed to use one additional concomitant, preventive medication.

The study excluded patients with a history of significant cardiovascular disease, vascular ischemia, or thrombotic events, such as cerebrovascular accident, transient ischemic attacks, deep vein thrombosis, or pulmonary embolism.

The primary efficacy endpoint was the mean change from baseline in the monthly average number of headache days of at least moderate severity during the 3-month treatment period. The secondary endpoints were the mean change from baseline in the monthly average number of migraine days during the 3-month treatment period, the proportion of patients reaching at least 50% reduction in the monthly average number of headache days of at least moderate severity during the 3-month treatment period, the mean change from baseline in the monthly average number of days of use of any acute headache medication during the 3-month treatment period, and the mean change from baseline in the number of headache days of at least moderate severity during the first month of treatment.

In Study 2, a total of 1130 patients (991 females, 139 males), ranging in age from 18 to 70 years, were randomized. A total of 1034 patients completed the 3-month double-blind phase.

Both monthly and quarterly dosing regimens of AJOVY treatment demonstrated statistically significant improvement for key efficacy outcomes compared to placebo, as summarized in Table 4.

Table 4: Efficacy Endpoints in Study 2
Study 2 Efficacy Endpoint | AJOVY 225 mga Monthly (N=375) | AJOVY 675 mg Quarterly (N=375) | Placebo (N=371)
Baseline headache days of any severityb | 20.3 | 20.4 | 20.3
Baseline headache days of at least moderate severityc | 12.8 | 13.2 | 13.3
Change from baseline in the monthly average number of headache days of at least moderate severity | -4.6 | -4.3 | -2.5
Difference from placebo | -2.1 | -1.8
p-value | <0.001 | <0.001
Change from baseline in the monthly average number of migraine days in patients | -5.0 | -4.9 | -3.2
Change from baseline in monthly average number of headache days of at least moderate severity at 4 weeks after 1st dose | -4.6 | -4.6 | -2.3
Percentage of patients with ≥ 50% reduction in monthly average number of headache days of at least moderate severity | 40.8% | 37.6% | 18.1%
Change from baseline in monthly average number of days of acute headache medication | -4.2 | -3.7 | -1.9

aIn Study 2, patients received a 675 mg starting dose.
bUsed for chronic migraine diagnosis.
cUsed for primary endpoint analysis.

Figure 3 displays the mean change from baseline in the average monthly number of headache days of at least moderate severity in Study 2.

Figure 3: Change from Baseline in Monthly Headache Days of At Least Moderate Severity in Study 2a

Figure 4 shows the distribution of change from baseline in monthly headache days of at least moderate severity at month 3 in bins of 3 days by treatment group. A treatment benefit over placebo for both dosing regimens of AJOVY is seen across a range of changes from baseline in headache days.

Figure 4: Distribution of Mean Change from Baseline in Monthly Headache Days of At Least Moderate Severity by Treatment Group in Study 2

*In Study 2, patients received a 675 mg starting dose.

Pediatric Patients 6 to 17 Years of Age

The efficacy of AJOVY for the preventive treatment of episodic migraine in pediatric patients 6 to 17 years of age was evaluated in a multicenter, randomized, 3-month, double-blind, placebo-controlled study (Study 3).

Episodic Migraine

Study 3 (NCT 04458857) included pediatric patients 6 to 17 years of age with a history of episodic migraine (patients with <15 headache days per month). All patients were randomized (1:1) to receive monthly subcutaneous injections of either AJOVY or placebo, over a 3-month period. Patients who weighed 45 kg or more received AJOVY 225 mg and patients who weighed under 45 kg received AJOVY 120 mg [see Dosage and Administration (2.1)]. Patients were allowed to use acute headache treatments during the study. A subset of patients (21%) was allowed to use up to two additional concomitant preventive medications. The study excluded patients with clinically significant cardiovascular disease.

The primary efficacy endpoint was the mean change from baseline in the monthly average number of migraine days during the 3-month treatment period. Secondary endpoints included the proportion of patients reaching at least a 50% reduction in monthly average number of migraine days during the 3-month treatment period; the mean change from baseline in the monthly average number of days of use of any acute headache medication during the 3-month treatment period; and the mean change from baseline in monthly average number of headache days of at least moderate severity during the 3-month treatment period.

In Study 3, a total of 235 patients (130 females, 105 males) were randomized. A total of 225 patients completed the 3-month, double-blind treatment period.

AJOVY demonstrated statistically significant improvements for efficacy endpoints compared to placebo over the 3-month period, as summarized in Table 5.

Table 5: Efficacy Endpoints in Study 3
Study 3 Efficacy Endpoint | AJOVY (N=123) | Placebo (N=111a)
Monthly migraine days (MMD)
Baseline migraine days | 7.8 | 7.5
Change from baseline | -2.5 | -1.4
Difference from placebo | -1.0
p-value | 0.021
≥50% MMD responders
% responders | 47.2% | 27.0%
Difference from placebo | 20.2%
p-value | 0.002
Monthly acute headache medication days
Change from baseline | -2.1 | -1.0
Difference from placebo | -1.1
p-value | 0.002
Monthly headache days of at least moderate severity
Change from baseline | -2.6 | -1.5
Difference from placebo | -1.1
p-value | 0.017

a One patient in the placebo group was excluded from the analysis due to not having at least 10 days of post-baseline efficacy data.

Figure 5 displays the mean change from baseline in the average monthly number of migraine days in Study 3.

Figure 5: Distribution of Change from Baseline in Mean Monthly Migraine Days by Placebo and Combined AJOVY Group (Full Analysis Set) in Study 3.

16 HOW SUPPLIED/STORAGE AND HANDLING

16.1 How Supplied

AJOVY (fremanezumab-vfrm) injection is a sterile, preservative-free, clear to opalescent, colorless to slightly yellow solution for subcutaneous administration.

AJOVY is not made with natural rubber latex.

AJOVY is supplied as follows:

Prefilled Autoinjector

- Pack of 1 autoinjector: 225 mg/1.5 mL single-dose prefilled autoinjector
  NDC 51759-202-10
- Pack of 3 autoinjectors: 3 x 225 mg/1.5mL single-dose prefilled autoinjectors
  NDC 51759-202-22

Prefilled Syringe

- Pack of 1 syringe: 225 mg/1.5 mL single-dose prefilled syringe
  NDC 51759-204-10

16.2 Storage and Handling

- Store refrigerated at 2°C to 8°C (36°F to 46°F) in the original outer carton to protect from light.
- If necessary, AJOVY may be kept in the original carton at room temperature up to 30°C (86°F) for a maximum of 7 days. After removal from the refrigerator, AJOVY must be used within 7 days or discarded. Once stored at room temperature, do not place back in the refrigerator.
- Do not freeze.
- Do not expose to extreme heat or direct sunlight.
- Do not shake.

17 PATIENT COUNSELING INFORMATION

Advise the patient and/or caregiver to read the FDA-approved patient labeling (Patient Information and Instructions for Use).

Information on Preparation and Administration

Instruct patients who are 13 years and older and/or caregivers on proper subcutaneous administration technique, including aseptic technique, and how to use the single-dose prefilled syringe [see Dosage and Administration (2.2)]. Instruct patients and/or caregivers to read and follow the Instructions for Use each time they use AJOVY.

Instruct patients who are prescribed the regimen of 675 mg every 3 months to administer the dosage as three consecutive subcutaneous injections of 225 mg each [see Dosage and Administration (2.1)].

Hypersensitivity Reactions

Inform patients about the signs and symptoms of hypersensitivity reactions and that these reactions can occur up to 1 month after administration. Advise patients to contact their healthcare provider if signs or symptoms of hypersensitivity reactions occur and to seek immediate medical attention if they experience serious or severe hypersensitivity reactions [see Warnings and Precautions (5.1)].

Hypertension

Inform patients that hypertension can develop or pre-existing hypertension can worsen with AJOVY, and that they should contact their healthcare provider if they experience elevation in their blood pressure [see Warnings and Precautions (5.2)].

Raynaud's Phenomenon

Inform patients that Raynaud’s phenomenon can develop or worsen with AJOVY. Advise patients to discontinue AJOVY and contact their healthcare provider if they experience signs or symptoms of Raynaud’s phenomenon [see Warnings and Precautions (5.3)].

Pregnancy

Advise women that there is a pregnancy exposure registry that monitors pregnancy outcomes in women exposed to AJOVY during pregnancy [see Use in Specific Populations (8.1)].

Manufactured by:
Teva Pharmaceuticals USA, Inc.
North Wales, PA 19454
US License No. 2016

AJOVY® (fremanezumab-vfrm), its use, or its process of manufacture, may be protected by one or more United States patents, including US 8,007,794, US 8,586,045, US 9,896,502, US 10,519,224, and US 10,899,826.

©2025 Teva Pharmaceuticals USA, Inc.

AJO-012

Patient Information

AJOVY® (a-JO-vee)

(fremanezumab-vfrm) injection

for subcutaneous use

What is AJOVY?

AJOVY is a prescription medicine used for the preventive treatment of:

- migraine in adults

- episodic migraine in children who are 6 to 17 years of age and who weigh 99 pounds (45 kg) or more.

It is not known if AJOVY is safe and effective in children under 6 years of age.

Who should not use AJOVY?

Do not use AJOVY if you are allergic to fremanezumab-vfrm or any of the ingredients in AJOVY. See the end of this leaflet for a complete list of the ingredients in AJOVY.

Before you use AJOVY, tell your healthcare provider if you:

- have high blood pressure.

- have circulation problems in your fingers and toes.

- are pregnant or plan to become pregnant. It is not known if AJOVY will harm your unborn baby.

Pregnancy Registry: There is a registry for women who become pregnant during treatment with AJOVY. The purpose of this registry is to collect information about the safety of AJOVY during pregnancy. Contact the registry as soon as you learn that you are pregnant or ask your healthcare provider to contact the registry for you. You or your healthcare provider can get information and enroll you in the registry by calling 1-833-927-2605 or visiting www.tevamigrainepregnancyregistry.com.

- are breastfeeding or plan to breastfeed. It is not known if AJOVY passes into your breast milk. Talk to your healthcare provider about the best way to feed your baby while using AJOVY.

Tell your healthcare provider about all the medicines you take, including prescription and over-the-counter medicines, vitamins, and herbal supplements.

Know the medicines you take. Keep a list of your medicines with you to show your healthcare provider and pharmacist when you get a new medicine.

How should I use AJOVY?

- See the detailed Instructions for Use for information on how to prepare and inject a dose of AJOVY.
- Use AJOVY exactly as your healthcare provider tells you to use it.
- AJOVY is given by injection under your skin (subcutaneously).
- Your healthcare provider should show you or your caregiver how to prepare and inject your dose of AJOVY before you or your caregiver give your AJOVY the first time.
- Your healthcare provider will tell you how much AJOVY to use and when to use it.
  - Adults: Your healthcare provider will tell you if you should use AJOVY 225 mg one time every month or AJOVY 675 mg one time every 3 months. If your prescribed dose is AJOVY 675 mg every 3 months, you must use 3 separate autoinjectors or 3 separate syringes. You will give 3 separate injections one time every 3 months. If you are giving 3 injections of AJOVY for your prescribed dose, you may use the same injection area for all 3 injections, but not the same spot.
  - Children 6 to 17 years of age who weigh 99 pounds (45 kg) or more: Use AJOVY 225 mg one time every month.
- Do not inject AJOVY in the same injection site that you inject other medicine.
- If you are switching from using AJOVY one time every month to one time every 3 months or if you are switching from using AJOVY one time every 3 months to one time every month, give the first dose of AJOVY on the day it was due to be given on your old schedule.
- If you miss a dose of AJOVY, take it as soon as possible. If you need to take the dose late, you will need to change your schedule: if you take 225 mg of AJOVY, inject your next dose 1 month after the late dose. If you take 675 mg of AJOVY, inject your next dose 3 months after the late dose. If you have questions about your schedule, ask your healthcare provider.

What are the possible side effects of AJOVY?

AJOVY may cause serious side effects, including:

- Allergic reactions. Allergic reactions, including itching, rash, and hives, can happen within hours and up to 1 month after receiving AJOVY. Call your healthcare provider or get emergency medical help right away if you have any of the following symptoms of an allergic reaction:
  - swelling of your face, mouth, tongue, or throat
  - trouble breathing

- High blood pressure. High blood pressure or worsening of high blood pressure can happen after receiving AJOVY. Contact your healthcare provider if you have an increase in blood pressure.
- Raynaud's phenomenon. A type of circulation problem can happen or worsen after receiving AJOVY. Symptoms may include:
  - fingers or toes may feel numb, cool, or painful
  - fingers and toes may change color from pale, to blue, to red
  Stop taking AJOVY and contact your healthcare provider if these symptoms occur.

The most common side effects of AJOVY include:

- injection site reactions

Tell your healthcare provider if you have any side effect that bothers you or that does not go away.

These are not all the possible side effects of AJOVY. For more information, ask your healthcare provider or pharmacist.

Call your doctor for medical advice about side effects. You may report side effects to FDA at 1-800-FDA-1088.

How should I store AJOVY?

- Store AJOVY in the refrigerator between 36°F to 46°F (2°C to 8°C).
- Keep AJOVY in the carton it comes in to protect from light.
- If needed, AJOVY may be stored at room temperature up to 86°F (30°C) in the carton it comes in for up to 7 days. Do not use AJOVY if it has been out of the refrigerator for 7 days or longer. Throw away (dispose of) AJOVY in a sharps disposal or puncture-resistant container if it has been out of the refrigerator for 7 days or longer. If stored at room temperature, do not place back in the refrigerator.
- Do not freeze. If AJOVY freezes, throw it away in a sharps disposal container.
- Keep AJOVY out of extreme heat and direct sunlight.
- Do not shake AJOVY.

Keep AJOVY prefilled autoinjector and AJOVY prefilled syringe out of the reach of small children.

General information about the safe and effective use of AJOVY.

Medicines are sometimes prescribed for purposes other than those listed in a Patient Information leaflet. Do not use AJOVY for a condition for which it was not prescribed. Do not give AJOVY to other people, even if they have the same symptoms that you have. It may harm them. You can ask your pharmacist or healthcare provider for information about AJOVY that is written for health professionals.

What are the ingredients in AJOVY?

Active ingredient: fremanezumab-vfrm

Inactive ingredients: disodium ethylenediaminetetraacetic acid dihydrate (EDTA), L-histidine, L-histidine hydrochloride monohydrate, polysorbate-80, sucrose, and Water for Injection.

AJOVY prefilled syringe and prefilled autoinjector are not made with natural rubber latex.

Manufactured by: Teva Pharmaceuticals USA, Inc., North Wales, PA 19454

US License No. 2016

AJOPL-007

For more information, go to www.AJOVY.com or call 1-888-483-8279.

This Patient Information has been approved by the U.S. Food and Drug Administration Revised: 8/2025

Instructions for Use

AJOVY® (a-JO-vee)
(fremanezumab-vfrm) injection
prefilled autoinjector, for subcutaneous use

For subcutaneous injection only.

Read and follow the Instructions for Use for your AJOVY prefilled autoinjector before you start using it and each time you get a refill.

Important:

- AJOVY prefilled autoinjector is for single-time (one-time) use only. Put AJOVY in a FDA-cleared sharps disposal or puncture-resistant container right away after use. Do not throw away (dispose of) your used sharps disposal container in your household trash.
- Before injecting, let AJOVY sit at room temperature for 30 minutes.
- Keep AJOVY prefilled autoinjector out of the reach of small children.
- After you remove the protective cap from AJOVY, to prevent infection, do not touch the needle.
- Do not inject AJOVY in your veins (intravenously).
- Do not re-use your AJOVY prefilled autoinjector as this could cause injury or infection.
- Do not share your AJOVY prefilled autoinjector with another person. You may give another person an infection or get an infection from them.

You or your caregiver may give AJOVY. You should not get your first dose of AJOVY until you or your caregiver receive training from a healthcare provider on the right way to use AJOVY.

Storage Conditions:

- Store AJOVY in the refrigerator between 36°F to 46°F (2°C to 8°C).
- Keep AJOVY in the carton it comes in to protect from light.
- If needed, AJOVY may be stored at room temperature up to 86°F (30°C) in the carton it comes in for up to 7 days. Do not use AJOVY if it has been out of the refrigerator for 7 days or longer. Throw away (dispose of) AJOVY in a sharps disposal or puncture-resistant container if it has been out of the refrigerator for 7 days or longer. Once stored at room temperature, do not place back in the refrigerator.
- Do not freeze. If AJOVY freezes, throw it away in a sharps disposal container.
- Keep AJOVY out of extreme heat and direct sunlight.

Do not shake AJOVY.

AJOVY prefilled autoinjector (Before use). See Figure A.

Figure A

AJOVY prefilled autoinjector (After use). See Figure B.

Figure B

- The blue plunger moves down the viewing window during the injection. The blue plunger fills the window when the injection is complete. Note: When the blue plunger has filled the viewing window you will still be able to see the gray stopper, as shown in Figure B.
- When injecting AJOVY, hold the prefilled autoinjector so that your hand does not cover the viewing window.

Read this before you inject.

Step 1. Check the dose your healthcare provider has prescribed.

AJOVY comes as a single-dose (one time) prefilled autoinjector. Your healthcare provider will prescribe the dose that is best for you.

- If your healthcare provider has prescribed 225 mg of AJOVY each month for you, give 1 injection each month, using a 225 mg prefilled AJOVY autoinjector.
- If your healthcare provider has prescribed 675 mg of AJOVY every 3 months for you, give 3 separate injections, one after another, using a different 225 mg prefilled AJOVY autoinjector for each injection. Give these injections 1 time every 3 months.

Before you inject, always check the label of your single-dose prefilled autoinjector to make sure you have the correct medicine and the correct dose of AJOVY. If you are not sure of your dose, ask your healthcare provider.

How do I inject AJOVY?

Step 2. Remove the prefilled autoinjector from the carton.

- You may need to use more than 1 prefilled autoinjector depending on your prescribed dose.
- Remove the autoinjector from the carton (see Figure C).
- Do not shake the prefilled autoinjector at any time, as this could affect the way the medicine works.

Important: If there are any unused autoinjectors left in the carton, put the carton and unused autoinjectors back in the refrigerator.

Figure C

Step 3. Gather the supplies you will need to inject AJOVY.

- Gather the following supplies (see Figure D) and the number of AJOVY 225 mg prefilled autoinjectors you will need to give your prescribed dose:

- If your dose is 225 mg, you will need 1 AJOVY 225 mg prefilled autoinjector.

- If your dose is 675 mg, you will need 3 AJOVY 225 mg prefilled autoinjectors.

- Alcohol swabs (not supplied).

- Gauze pads or cotton balls (not supplied).

- Sharps disposal or puncture-resistant container (not supplied).

Figure D

Step 4. Let AJOVY reach room temperature.

- Place the supplies you have gathered on a clean, flat surface.
- Wait for 30 minutes to allow the medicine to reach room temperature.
- Do not leave the prefilled autoinjector in direct sunlight.
- Do not warm up the AJOVY prefilled autoinjector using a heat source such as hot water or a microwave.

Step 5. Wash your hands.

- Wash your hands with soap and water and dry well with a clean towel. Be careful not to touch your face or hair after washing your hands.

Step 6. Look closely at your AJOVY prefilled autoinjector.

Note: You may see air bubbles in the prefilled autoinjector. This is normal. Do not remove the air bubbles from the prefilled autoinjector before giving your injection.

Injecting AJOVY with these air bubbles will not harm you.

- Check that the liquid medicine in the prefilled autoinjector viewing window is clear and colorless to slightly yellow before you give your injection. (See Figure E). If the liquid has any particles in it, or is discolored, cloudy, or frozen, do not use the prefilled autoinjector. Call your healthcare provider or pharmacist. | - Do not use the prefilled autoinjector if it has any visible damage, such as cracks or leaks. See disposal instructions in Step 12.
- Check that AJOVY appears on the prefilled autoinjector. | - Do not use if you have been given the wrong medicine.
- Check the expiration date (EXP) printed on the prefilled autoinjector label. | - Do not use the prefilled autoinjector if the expiration date (EXP) has passed.

Figure E

Step 7: Choose your injection area.

- Choose an injection area from the following areas (see Figure F):
  - your stomach area (abdomen), avoid about 2 inches around the belly button.
  - the front of your thighs, an area that is at least 2 inches above the knee and 2 inches below the groin.
  - the back of your upper arms, in the fleshy area of the upper back portion.

Figure F

Note: There are some injection areas on your body that are hard to reach (like the back of your arm). You may need help from someone who has been instructed on how to give your injection if you cannot reach certain injection areas.

Step 8. Clean your injection area.

- Clean the chosen injection area using a new alcohol swab. Let your skin dry.

- Do not inject AJOVY into an area that is tender, red, bruised, callused, tattooed, hard, or that has scars or stretch marks.

- Do not inject AJOVY in the same injection site that you inject other medicine.
- If you want to use the same injection area for the 3 separate injections needed for the 675 mg dose, make sure the second and third injections are not at the same spot you used for the other injections.

Step 9. Remove protective cap and do not replace.

- Pick up the prefilled autoinjector in 1 hand.
- Hold the prefilled autoinjector as shown in Figure G and pull the protective cap straight off with your other hand. Do not twist.
- Throw away the protective cap right away.
- Do not put the protective cap back on the prefilled autoinjector, to avoid injury and infection.

Figure G

Step 10. Give your injection.

- 10.1 Place the prefilled autoinjector at a 90 degree angle against your skin at the injection site you have cleaned (see Figure H).

Figure H

10.2 Press down on the prefilled autoinjector and keep holding it down against the skin for about 30 seconds.

Do not remove pressure until the 3 steps below are complete.

1. You hear
the first “click”
(this means the injection has started and the blue plunger starts to move).

2. You hear
a second “click”
(about 15 seconds after the first click. The plunger will be moving to the bottom of the viewing window as the medicine is being injected.)

3. You wait
another 10 seconds.
(to make sure all the medicine is injected).

10.3 Check that the blue plunger has filled the viewing window and remove the autoinjector from the skin by lifting the prefilled autoinjector straight up (see Figure I).

Note: When the blue plunger has filled the viewing window you will be able to see the gray stopper.

As the prefilled autoinjector is lifted from the skin, the needle shield returns to the original (before use) position and locks into place, covering the needle.

Do not try to put the protective cap back on the used prefilled autoinjector as it is no longer needed.

Do not try to re-use the prefilled autoinjector.

Figure I

Step 11. Apply pressure to the injection site.

- Use a clean, dry cotton ball, or gauze pad to gently press on the injection site for a few seconds.
- Do not rub the injection site.

- Do not re-use the prefilled autoinjector.

Step 12. Dispose of your prefilled autoinjector right away.

- Put your used prefilled autoinjectors in a FDA-cleared sharps disposal container right away after use.
- Do not throw away (dispose of) prefilled autoinjectors in your household trash. Do not recycle your used sharps disposal container.
- If you do not have a FDA-cleared sharps disposal container, you may use a household container that is:
  - made of a heavy-duty plastic,
  - can be closed with a tight-fitting, puncture-resistant lid, without sharps being able to come out,
  - upright and stable during use,
  - leak-resistant, and
  - properly labeled to warn of hazardous waste inside the container.
- When your sharps disposal container is almost full, you will need to follow your community guidelines for the right way to dispose of your sharps disposal container. There may be state or local laws about how you should throw away used autoinjectors. For more information about safe sharps disposal, and for specific information about sharps disposal in the state that you live in, go to the FDA’s website at: http://www.fda.gov/safesharpsdisposal
- Do not dispose of your used sharps disposal container in your household trash unless your community guidelines permit this. Do not recycle your used sharps disposal container.

Injection Complete

This Instructions for Use has been approved by the U.S. Food and Drug Administration.

Manufactured by:
Teva Pharmaceuticals USA, Inc.
North Wales, PA 19454
US License No. 2016

©2025 Teva Pharmaceuticals USA, Inc.

AJOIFU-AI-005
Revised: 8/2025

Instructions for Use

AJOVY® (a-JO-vee)
(fremanezumab-vfrm) injection
prefilled syringe, for subcutaneous use

For subcutaneous injection only.

Read and follow the Instructions for Use for your AJOVY prefilled syringe before you start using it and each time you get a refill.

Important:

- AJOVY prefilled syringe is for single-time (one-time) use only. Put AJOVY in a FDA-cleared sharps disposal or puncture-resistant container right away after use. Do not throw away (dispose of) your used sharps disposal container in your household trash.
- Before injecting, let AJOVY sit at room temperature for 30 minutes.
- Keep AJOVY prefilled syringe out of the reach of small children.
- After you remove the needle cap from AJOVY, to prevent infection, do not touch the needle.
- Do not pull back on the plunger at any time, as this can break the prefilled syringe.
- Do not inject AJOVY in your veins (intravenously).
- Do not re-use your AJOVY prefilled syringe, as this could cause injury or infection.
- Do not share your AJOVY prefilled syringe with another person. You may give another person an infection or get an infection from them.

You or your caregiver may give AJOVY. You should not get your first dose of AJOVY until you or your caregiver receive training from a healthcare provider on the right way to use AJOVY.

Storage Conditions:

- Store AJOVY in the refrigerator between 36°F to 46°F (2°C to 8°C).
- Keep AJOVY in the carton it comes in to protect from light.
- If needed, AJOVY may be stored at room temperature up to 86°F (30°C) in the carton it comes in for up to 7 days. Do not use AJOVY if it has been out of the refrigerator for 7 days or longer. Throw away (dispose of) AJOVY in a sharps disposal or puncture-resistant container if it has been out of the refrigerator for 7 days or longer. Once stored at room temperature, do not place back in the refrigerator.
- Do not freeze. If AJOVY freezes, throw it away in a sharps disposal container.
- Keep AJOVY out of extreme heat and direct sunlight.
- Do not shake AJOVY.

AJOVY prefilled syringe (Before use). See Figure A.

Figure A

AJOVY prefilled syringe (After use). See Figure B.

Figure B

Read this before you inject.

Step 1. Check the dose your healthcare provider has prescribed.

AJOVY comes as a single-dose (one time) prefilled syringe. Your healthcare provider will prescribe the dose that is best for you.

- If your healthcare provider has prescribed 225 mg of AJOVY each month for you, give 1 injection each month using a 225 mg prefilled AJOVY syringe.

- If your healthcare provider has prescribed 675 mg of AJOVY every 3 months for you, give 3 separate injections, one after another, using a different 225 mg prefilled AJOVY syringe for each injection. Give these injections 1 time every 3 months.

Before you inject, always check the label of your single-dose prefilled syringe to make sure you have the correct medicine and the correct dose of AJOVY. If you are not sure of your dose, ask your healthcare provider.

How do I inject AJOVY?

Step 2. Remove the prefilled syringe from the carton.

- You may need to use more than 1 prefilled syringe depending on your prescribed dose.
- Hold the prefilled syringe (see Figure C).
- Remove the syringe from the carton.
- Do not shake the prefilled syringe at any time, as this could affect the way the medicine works.

Figure C

Step 3. Gather the supplies you will need to inject AJOVY.

- Gather the following supplies (see Figure D) and the number of AJOVY 225 mg prefilled syringes you will need to give your prescribed dose:

- If your dose is 225 mg, you will need 1 AJOVY 225 mg prefilled syringe.

- If your dose is 675 mg, you will need 3 AJOVY 225 mg prefilled syringes.

- alcohol swabs (not supplied).

- gauze pads or cotton balls (not supplied).

- sharps disposal or puncture-resistant container (not supplied).

Figure D

Step 4. Let AJOVY reach room temperature.

- Place the supplies you have gathered on a clean, flat surface.
- Wait for 30 minutes to allow the medicine to reach room temperature.
- Do not leave the prefilled syringe in direct sunlight.
- Do not warm up the AJOVY prefilled syringe using a heat source such as hot water or a microwave.

Step 5. Wash your hands.

- Wash your hands with soap and water and dry well with a clean towel. Be careful not to touch your face or hair after washing your hands.

Step 6. Look closely at your AJOVY prefilled syringe.

Note: You may see air bubbles in the prefilled syringe. This is normal. Do not remove the air bubbles from the prefilled syringe before giving your injection. Injecting AJOVY with these air bubbles will not harm you.

- Check that the liquid medicine in the prefilled syringe is clear and colorless to slightly yellow before you give your injection (see Figure E). If the liquid has any particles in it, or is discolored, cloudy, or frozen, do not use the prefilled syringe. Call your healthcare provider or pharmacist. | - Do not use the prefilled syringe if it has any visible damage, such as cracks or leaks. See disposal instructions in Step 13.
- Check that AJOVY appears on the prefilled syringe. | - Do not use if you have been given the wrong medicine.
- Check the expiration date (EXP) printed on the prefilled syringe label. | - Do not use the prefilled syringe if the expiration date (EXP) has passed.

Figure E

Step 7. Choose your injection area.

- Choose an injection area from the following areas (see Figure F):

- your stomach area (abdomen), avoid about 2 inches around the belly button.
- the front of your thighs, an area that is at least 2 inches above the knee and 2 inches below the groin.
- the back of your upper arms, in the fleshy area of the upper back portion.

Figure F

Note: There are some injection areas on your body that are hard to reach (like the back of your arm). You may need help from someone who has been instructed on how to give your injection if you cannot reach certain injection areas.

Step 8. Clean your injection area.

- Clean the chosen injection area using a new alcohol swab. Let your skin dry.
- Do not inject AJOVY into an area that is tender, red, bruised, callused, tattooed, hard, or that has scars or stretch marks.
- Do not inject AJOVY in the same injection site that you inject other medicine.
- If you want to use the same injection area for the 3 separate injections needed for the 675 mg dose, make sure the second and third injections are not at the same spot you used for the other injections.

Step 9. Remove needle cap and do not replace.

- Pick up the body of the prefilled syringe with 1 hand.
- Pull the needle cap straight off with your other hand (see Figure G). Do not twist.
- Throw away the needle cap right away.
- Do not put the needle cap back on the prefilled syringe, to avoid injury and infection.

Figure G

Step 10. Give your injection following the 4 steps below.

1. Use your free hand to gently pinch up at least 1 inch of the skin that you have cleaned.

2. Insert the needle into the pinched skin at a 45 to 90 degree angle.

3. When the needle is all the way into your skin, use your thumb to push the plunger.

4. Push the plunger slowly all the way down as far as it will go to inject all of the medicine.

Step 11. Remove the needle from your skin.

- After you have injected all of the medicine, pull the needle straight out (see Figure H).
- Do not recap the needle at any time to avoid injury and infection.

Figure H

Step 12. Apply pressure to the injection site.

- Use a clean, dry cotton ball or gauze to gently press on the injection site for a few seconds.
- Do not rub the injection site.
- Do not re-use the prefilled syringe.

Step 13. Dispose of your prefilled syringe right away.

- Put your used prefilled syringes, needles, and sharps in a FDA-cleared sharps disposal container right away after use.
- Do not throw away (dispose of) loose needles, syringes, or prefilled syringes in your household trash. Do not recycle your used sharps disposal container.
- If you do not have a FDA-cleared sharps disposal container, you may use a household container that is:

- made of a heavy-duty plastic,
- can be closed with a tight-fitting, puncture-resistant lid, without sharps being able to come out,
- upright and stable during use,
- leak-resistant, and
- properly labeled to warn of hazardous waste inside the container.

- When your sharps disposal container is almost full, you will need to follow your community guidelines for the right way to dispose of your sharps disposal container. There may be state or local laws about how you should throw away used syringes. For more information about safe sharps disposal, and for specific information about sharps disposal in the state that you live in, go to the FDA’s website at: http://www.fda.gov/safesharpsdisposal
- Do not dispose of your used sharps disposal container in your household trash unless your community guidelines permit this. Do not recycle your used sharps disposal container.

Injection Complete

This Instructions for Use has been approved by the U.S. Food and Drug Administration.

Manufactured by:
Teva Pharmaceuticals USA, Inc.
North Wales, PA 19454
US License No. 2016

©2025 Teva Pharmaceuticals USA, Inc.

AJOIFU-PFS-005

Revised: 8/2025

PACKAGE/LABEL DISPLAY PANEL,Carton of 1 prefilled syringe

NDC 51759-204-10
Rx only
AJOVY® (fremanezumab-vfrm) injection 225 mg/1.5 mL
FOR SUBCUTANEOUS USE ONLY
One single-dose prefilled syringe
Store in refrigerator at 36°F to 46°F (2° to 8°C) in the original carton to protect from light. DO NOT FREEZE. DO NOT SHAKE. If needed, AJOVY® may be kept at room temperature up to 86°F (30°C) for 7 days. Once stored at room temperature, do not place back in the refrigerator. Discard after 7 days.

OPEN HERE
teva

PACKAGE/LABEL DISPLAY PANEL,Carton of 1 prefilled autoinjector

NDC 51759-202-10
Rx only
AJOVY (fremanezumab-vfrm) injection 225 mg/1.5 mL
FOR SUBCUTANEOUS USE ONLY
One single-dose prefilled autoinjector
Store in refrigerator at 36°F to 46°F (2° to 8°C) in the original carton to protect from light. DO NOT FREEZE. DO NOT SHAKE. If needed, AJOVY® may be kept at room temperature up to 86°F (30°C) for 7 days. Once stored at room temperature, do not place back in the refrigerator. Discard after 7 days.

OPEN HERE
teva

PACKAGE/LABEL DISPLAY PANEL,Carton of 3 prefilled autoinjectors

NDC 51759-202-22
Rx only
AJOVY (fremanezumab-vfrm) injection 225 mg/1.5 mL
FOR SUBCUTANEOUS USE ONLY
3 x 225 mg/1.5 mL single-dose prefilled autoinjectors
Store in refrigerator at 36°F to 46°F (2° to 8°C) in the original carton to protect from light. DO NOT FREEZE. DO NOT SHAKE. If needed, AJOVY® may be kept at room temperature up to 86°F (30°C) for 7 days. Once stored at room temperature, do not place back in the refrigerator. Discard after 7 days.

OPEN HERE
teva